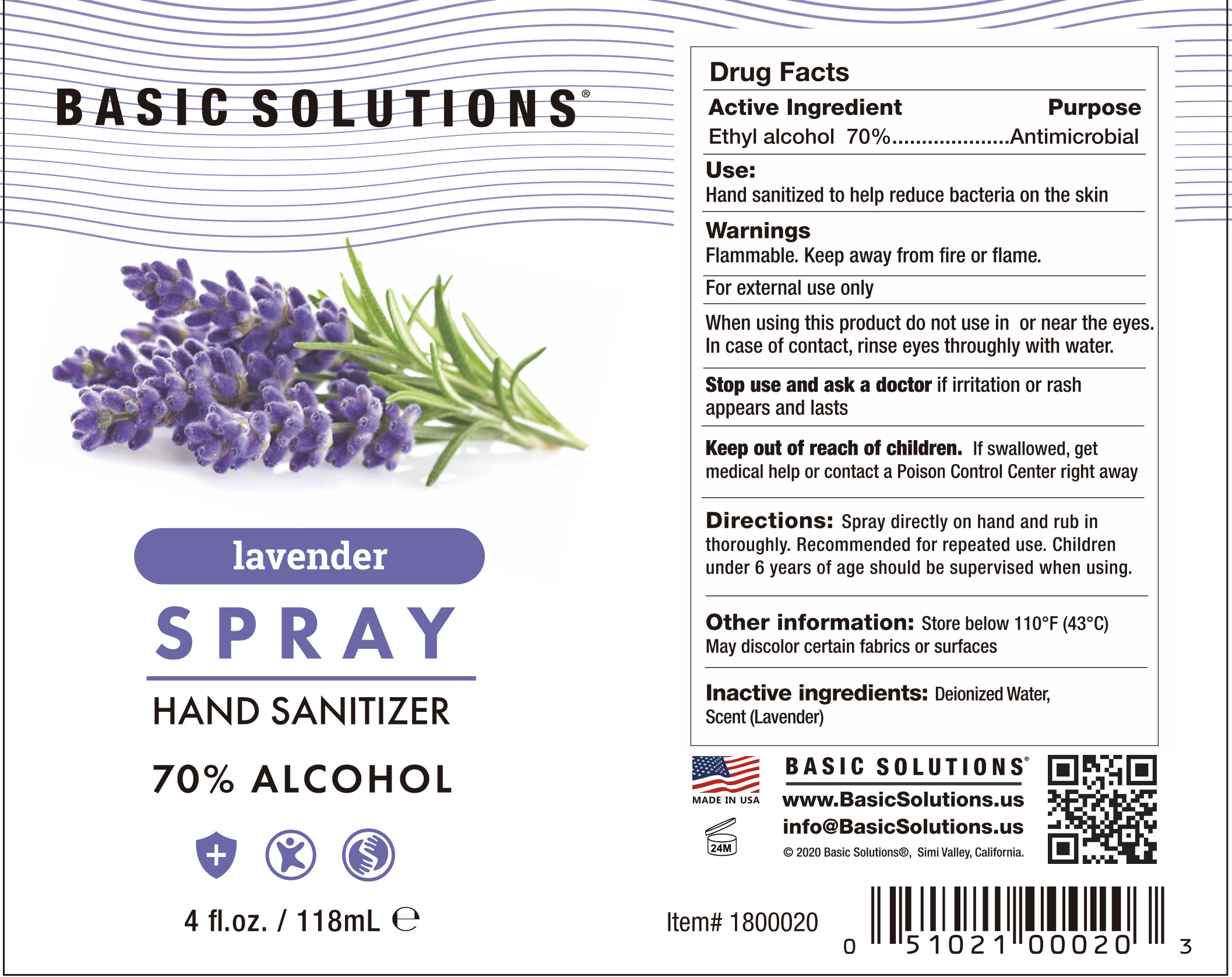 DRUG LABEL: Basic Solutions Hand SanitizerSpray 4 oz lavender
NDC: 69797-009 | Form: SPRAY
Manufacturer: Wsm Investments, LLC Topco Sales
Category: otc | Type: HUMAN OTC DRUG LABEL
Date: 20200610

ACTIVE INGREDIENTS: ALCOHOL 82.6 mL/118 mL
INACTIVE INGREDIENTS: WATER; LAVENDER JOBFISH WHOLE

DOSAGE AND ADMINISTRATION

Store below 110°F (43°C)

INACTIVE INGREDIENT

Deionized Water、Scan(lavender)

INDICATIONS AND USAGE

Spray directly on hand and rub in thoroughly. Recommended for repeated use.

ACTIVE INGREDIENT

Ethyl alcohol

keep out of reach of children

PURPOSE

Disinfection
Sterilization
No Rinseing

WARNINGS

Flammable. Keep away from fire or flame.